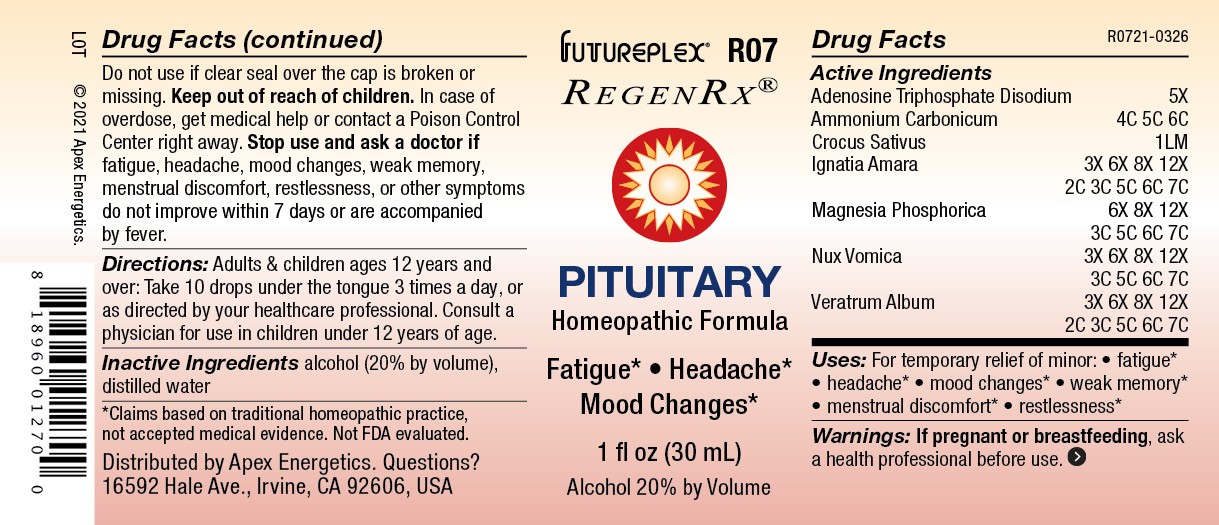 DRUG LABEL: R07
NDC: 63479-1807 | Form: SOLUTION
Manufacturer: Apex Energetics Inc.
Category: homeopathic | Type: HUMAN OTC DRUG LABEL
Date: 20240108

ACTIVE INGREDIENTS: ADENOSINE TRIPHOSPHATE DISODIUM 5 [hp_X]/1 mL; AMMONIUM CARBONATE 6 [hp_C]/1 mL; SAFFRON 1 [hp_Q]/1 mL; STRYCHNOS IGNATII SEED 7 [hp_C]/1 mL; MAGNESIUM PHOSPHATE, DIBASIC TRIHYDRATE 7 [hp_C]/1 mL; STRYCHNOS NUX-VOMICA SEED 7 [hp_C]/1 mL; VERATRUM ALBUM ROOT 7 [hp_C]/1 mL
INACTIVE INGREDIENTS: ALCOHOL; WATER

R07

Active Ingredients
Adenosine Triphosphate Disodium | 5X
Ammonium Carbonicum | 4C 5C 6C
Crocus Sativus | 1LM
Ignatia Amara | 3X 6X 8X 12X 2C 3C 5C 6C 7C
Magnesia Phosphorica | 6X 8X 12X 3C 5C 6C 7C
Nux Vomica | 3X 6X 8X 12X 3C 5C 6C 7C
Veratrum Album | 3X 6X 8X 12X 2C 3C 5C 6C 7C

INDICATIONS AND USAGE

Uses:

For temporary relief of minor:

fatigue*

headache*

mood changes*

weak memory*

menstrual discomfort*

restlessness*

*Claims based on traditional homeopathic practice, not accepted medical evidence. Not FDA evaluated.

Warnings:

PREGNANCY OR BREAST FEEDING

If pregnant or breastfeeding, ask a health professional before use.

Do not use if clear seal over the cap is broken or missing.

Keep out of reach of children. In case of overdose, get medical help or contact a Poison Control Center right away.

Stop use and ask a doctor if fatigue, headache, mood changes, weak memory, menstrual discomfort, restlessness, or other symptoms do not improve within 7 days or are accompanied by fever.

Directions:

Adults & children ages 12 years and over: Take 10 drops under the tongue 3 times a day, or as directed by your healthcare professional. Consult a physician for use in children under 12 years of age.

Inactive Ingredients

alcohol (20% by volume), distilled water

Distributed by Apex Energetics. Questions?
16592 Hale Ave., Irvine, CA 92606, USA

PACKAGE LABEL

FUTUREPLEX® R07

REGENRX®

PITUITARY

Homeopathic Formula

Fatigue • Headache
Mood Changes

1 fl oz (30 mL)

Alcohol 20% by Volume